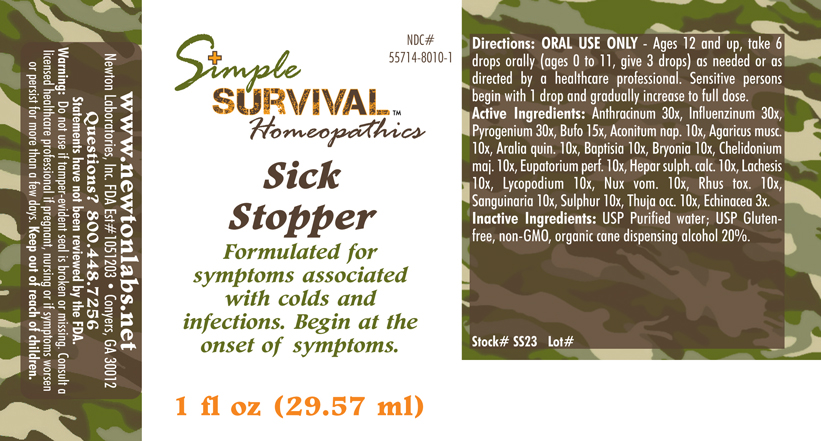 DRUG LABEL: Sick Stopper 
NDC: 55714-8010 | Form: LIQUID
Manufacturer: Newton Laboratories, Inc.
Category: homeopathic | Type: HUMAN OTC DRUG LABEL
Date: 20140415

ACTIVE INGREDIENTS: Bacillus Anthracis Immunoserum Rabbit 30 [hp_X]/1 mL; Influenza A Virus 30 [hp_X]/1 mL; Rancid Beef 30 [hp_X]/1 mL; Bufo Bufo Cutaneous Gland 15 [hp_X]/1 mL; Aconitum Napellus 10 [hp_X]/1 mL; Amanita Muscaria Var. Muscaria Fruiting Body 10 [hp_X]/1 mL; American Ginseng 10 [hp_X]/1 mL; Baptisia Tinctoria 10 [hp_X]/1 mL; Bryonia Alba Root 10 [hp_X]/1 mL; Chelidonium Majus 10 [hp_X]/1 mL; Eupatorium Perfoliatum Flowering Top 10 [hp_X]/1 mL; Calcium Sulfide 10 [hp_X]/1 mL; Lachesis Muta Venom 10 [hp_X]/1 mL; Lycopodium Clavatum Spore 10 [hp_X]/1 mL; Strychnos Nux-vomica Seed 10 [hp_X]/1 mL; Toxicodendron Pubescens Leaf 10 [hp_X]/1 mL; Sanguinaria Canadensis Root 10 [hp_X]/1 mL; Sulfur 10 [hp_X]/1 mL; Thuja Occidentalis Leafy Twig 10 [hp_X]/1 mL; Echinacea, Unspecified 3 [hp_X]/1 mL; Influenza B Virus 30 [hp_X]/1 mL
INACTIVE INGREDIENTS: Alcohol

Sick Stopper

INDICATIONS & USAGE SECTION

Sick Stopper Formulated for symptoms associated with colds and infections. Begin at the onset of symptoms.

DOSAGE & ADMINISTRATION SECTION

Directions: ORAL USE ONLY - Ages 12 and up, take 6 drops orally (ages 0 to 11, give 3 drops) as needed or as directed by a healthcare professional. Sensitive persons begin with 1 drop and gradually increase to full dose.

OTC - ACTIVE INGREDIENT SECTION

Anthracinum 30x, Influenzinum 30x, Pyrogenium 30x, Bufo 15x, Aconitum nap. 10x, Agaricus musc. 10x, Aralia quin. 10x, Baptisia 10x, Bryonia 10x, Chelidonium maj. 10x, Eupatorium perf. 10x, Hepar sulph. calc. 10x, Lachesis 10x, Lycopodium 10x, Nux vom. 10x, Rhus toxi. 10x, Sanguinaria 10x, Sulphur 10x, Thuja occ. 10x, Echinacea 3x.

OTC - PURPOSE SECTION

Formulated for symptoms associated with colds and infections. Begin at the onset of symptoms.

INACTIVE INGREDIENT SECTION

Inactive Ingredients: USP Purified Water; USP Gluten-free, non-GMO, organic cane dispensing alcohol 20%.

QUESTIONS SECTION

www.newtonlabs.net Newton Laboratories, Inc. FDA Est # 1051203 - Conyers, GA 30012
Questions? 1.800.448.7256

WARNINGS SECTION

Warning: Do not use if tamper - evident seal is broken or missing. Consult a licensed healthcare professional if pregnant, nursing or if symptoms worsen or persist for more than a few days. Keep out of reach of children.

OTC - PREGNANCY OR BREAST FEEDING SECTION

Consult a licensed healthcare professional if pregnant, nursing or if symptoms worsen or persist for more than a few days.

OTC - KEEP OUT OF REACH OF CHILDREN SECTION

Keep out of reach of children.